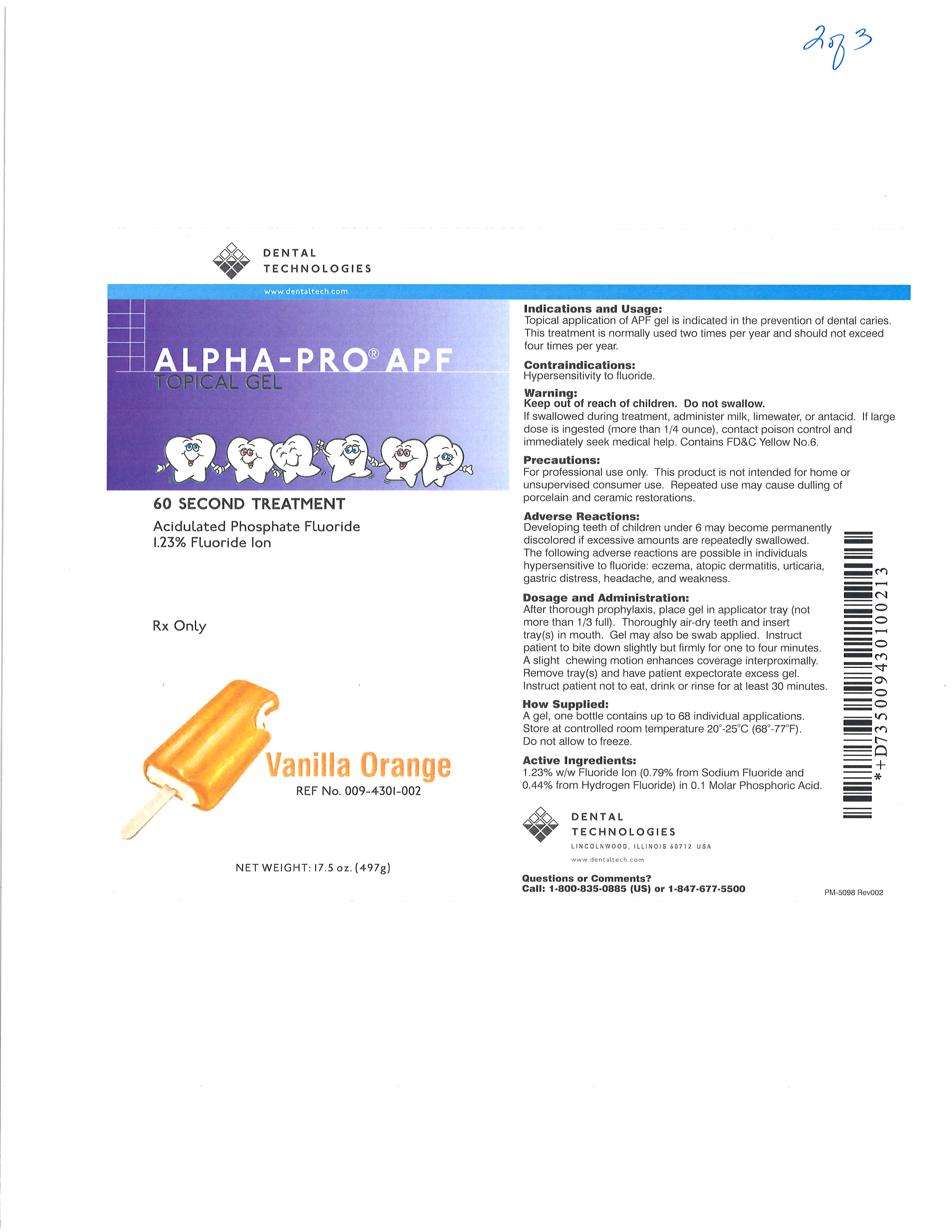 DRUG LABEL: Alpha-Pro
NDC: 55346-0943 | Form: GEL
Manufacturer: Dental Technologies, Inc.
Category: prescription | Type: HUMAN PRESCRIPTION DRUG LABEL
Date: 20251104

ACTIVE INGREDIENTS: SODIUM FLUORIDE 7.9 mg/1 g; HYDROFLUORIC ACID 4.4 mg/1 g

DTI APF - Vanilla Orange

Indications and Usage:

Topical application of APF gel is indicated in the prevention of dental caries. This treatment is normally used two times per year and should not exceed four times per year.

Contraindications:

Hypersensitivity to fluoride.

Warning:

Keep out of reach of children. Do not swallow.

If swallowed during treatment, administer milk, limewater, or antacid. If larger dose is ingested (more than 1/4 ounce), contact poison control and immediately seek medical help. Contains FD&C Yellow No.6.

Precautions:

For professional use only. This product is not intended for home or unsupervised consumer use. Repeated use may cause dulling of porcelain and ceramic restorations.

Adverse Reactions:

Developing teeth of children under age 6 may become permanently discolored if excessive amounts are repeatedly swallowed. The following adverse reactions are possible in individuals hypersensitive to fluoride: eczema, atopic dermatitis, urticaria, gastric distress, headache, and weakness.

Dosage and Administration:

After thorough prophylaxis, place gel in applicator tray (not more than 1/3 full). Throughly air-dry teeth and insert tray(s) in mouth. Gel may also be swab applied. Instruct patient to bite down slightly but firmly for one to four minutes. A slight chewing motion enhances coverage interproximally. Remove tray(s) and have patient expectorate excess gel. Instruct patient not to eat, drink or rinse for at least 30 minutes.

How Supplied:

A gel, one bottle contains up to 68 individual applications. Store at controlled room temperature 20°- 25°C (68°-77°F).

Do not allow to freeze.

Active Ingredients:

1.23% w/w Fluoride Ion (0.79% from Sodium Fluoride and 0.44% from Hydrogen Fluoride) in 0.1 Molar Phosphoric Acid.

DENTAL TECHNOLOGIES

LINCOLNWOOD, ILLINOIS 60712 USA

www.dentaltech.com

Questions or Comments?

Call: 1-800-835-0885 (US) or 1-847-677-5500

PM-5098 Rev002

Principal Display Panel

DENTAL TECHNOLOGIES

www.dentaltech.com

ALPHA-PRO® APF

TOPICAL GEL

60 SECOND TREATMENT

Acidulated Phosphate Fluoirde

1.23% Fluoride Ion

Rx Only

Vanilla Orange

REF No. 009-4301-002

NET WEIGHT: 17.5 oz. (497g)